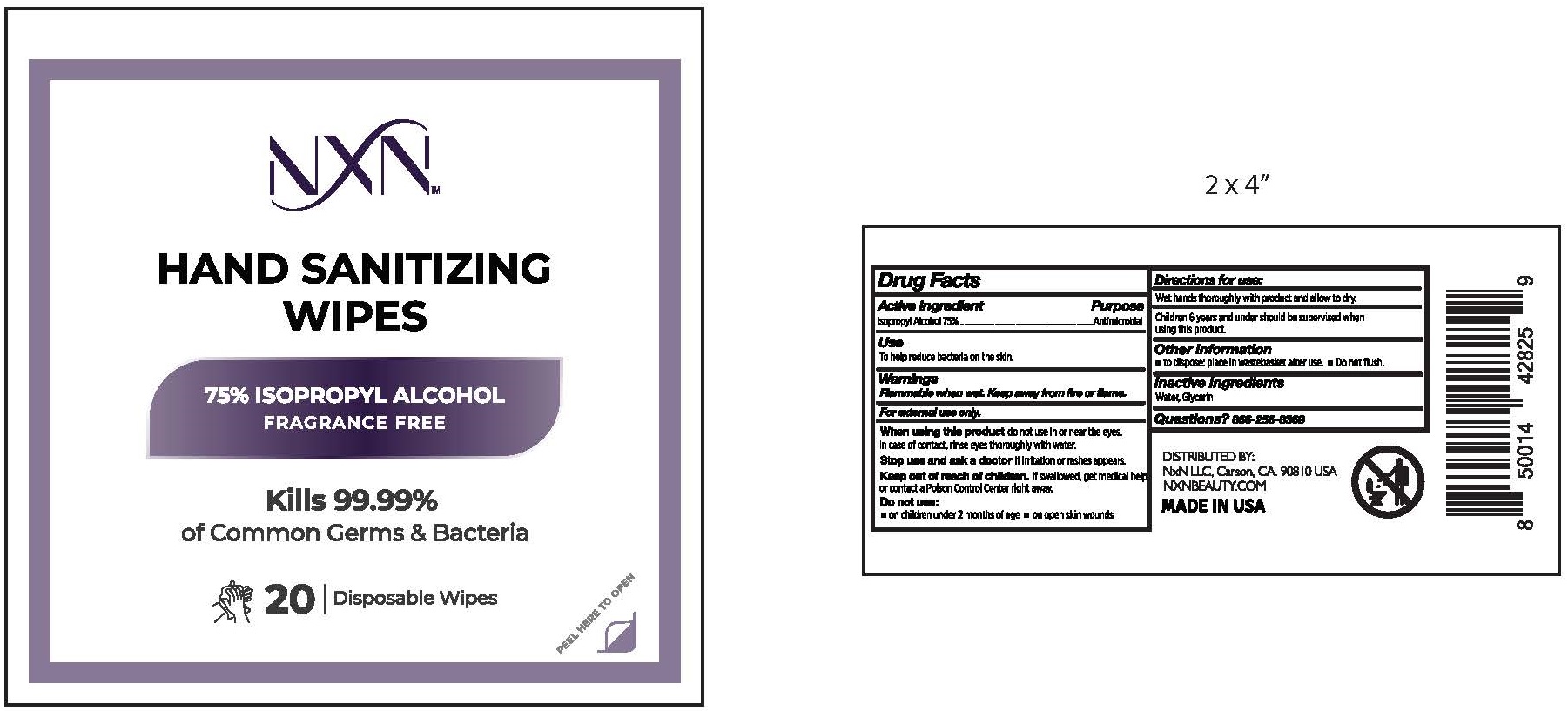 DRUG LABEL: NXN HAND SANITIZING WIPES

NDC: 77761-102 | Form: GEL
Manufacturer: NXN BEAUTY, LLC
Category: otc | Type: HUMAN OTC DRUG LABEL
Date: 20220413

ACTIVE INGREDIENTS: ISOPROPYL ALCOHOL 7.5 mL/1 1
INACTIVE INGREDIENTS: WATER; GLYCERIN

NXN - HAND SANITIZING WIPES - 75% ISOPROPYL ALCOHOL (77761-102)

ACTIVE INGREDIENT

ISOPROPYL ALCOHOL 75%

PURPOSE

ANTIMICROBIAL

USES

TO HELP REDUCE BACTERIA ON THE SKIN.

WARNINGS

Flammable when wet. Keep away from fire or flame.

For external use only.

WHEN USING THIS PRODUCT DO NOT USE IN OR NEAR THE EYES. IN CASE OF CONTACT, RINSE EYES THOROUGHLY WITH WATER.

STOP USE AND ASK A DOCTOR IF IRRITATION OR RASH APPEARS.

Keep out of reach of children. If swallowed, get medical help or contact a Poison Control Center right away.

Do not use:

- on children under 2 months of age
- on open skin wounds

DIRECTIONS

Wet hands thoroughly with product and allow to dry.

Children 6 years and under should be supervised when using product.

OTHER INFORMATION

- to dispose: place in wastebasket after use.
- Do not flush.

INACTIVE INGREDIENTS

WATER, GLYCERIN

QUESTIONS?

866-256-8369